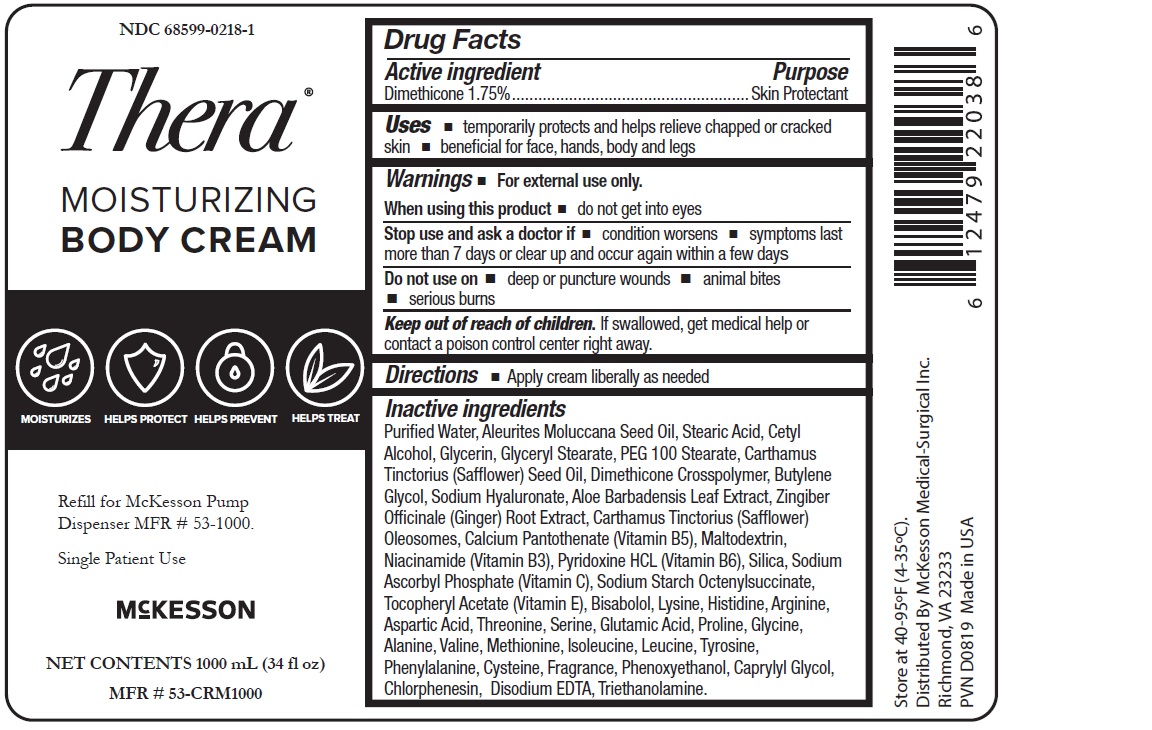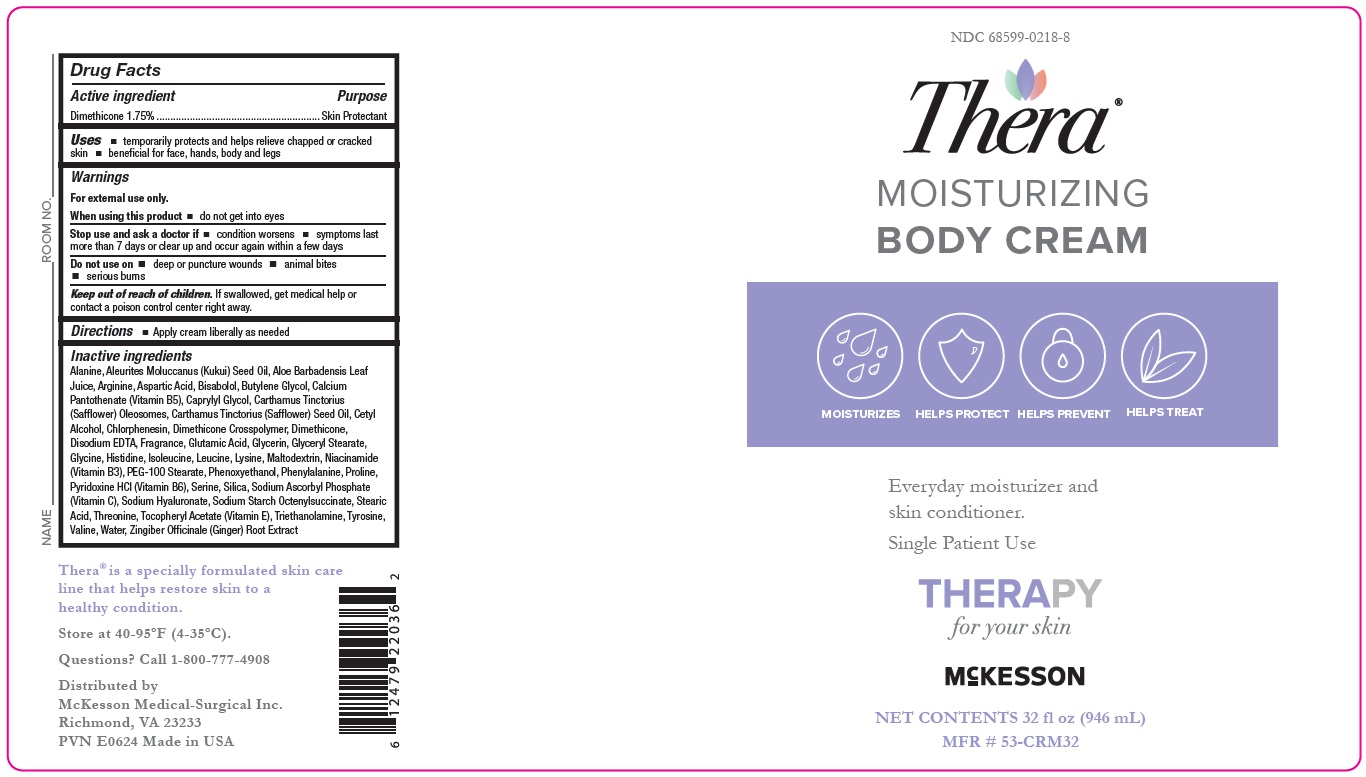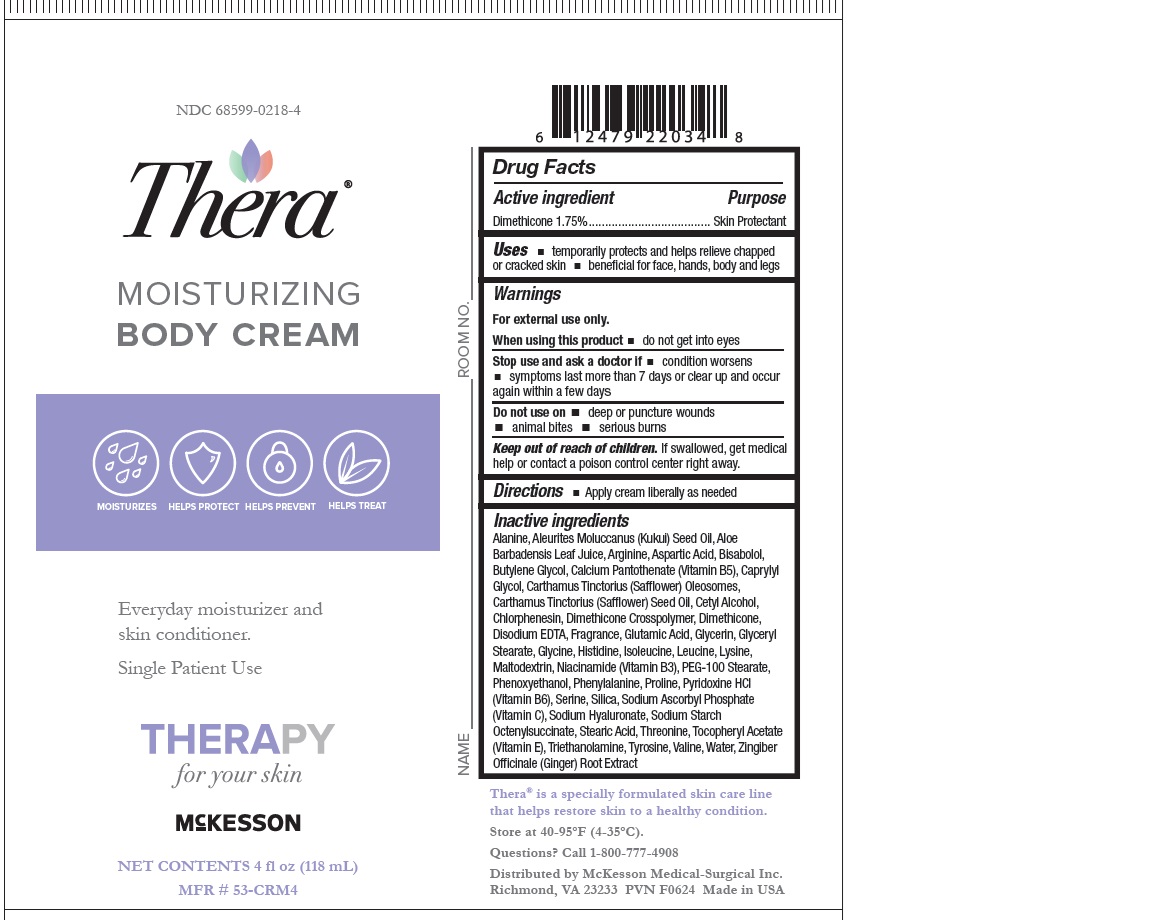 DRUG LABEL: Dimethicone
NDC: 68599-0218 | Form: CREAM
Manufacturer: McKesson
Category: otc | Type: HUMAN OTC DRUG LABEL
Date: 20240618

ACTIVE INGREDIENTS: DIMETHICONE 17.5 ug/1 mg
INACTIVE INGREDIENTS: OCTENYLSUCCINIC ACID; CARTHAMUS TINCTORIUS (SAFFLOWER) OLEOSOMES; LEVOMENOL; GLYCERYL MONOSTEARATE; EDETATE DISODIUM; KUKUI NUT OIL; STEARIC ACID; CETYL ALCOHOL; GINGER; CALCIUM PANTOTHENATE; PYRIDOXINE HYDROCHLORIDE; ARGININE; ASPARTIC ACID; PROLINE; SERINE; ALANINE; GLYCERIN; PEG-100 STEARATE; CARTHAMUS TINCTORIUS FLOWER OIL; DIMETHICONE CROSSPOLYMER (450000 MPA.S AT 12% IN CYCLOPENTASILOXANE); BUTYLENE GLYCOL; HYALURONATE SODIUM; WATER; NIACINAMIDE; .ALPHA.-TOCOPHEROL ACETATE; VALINE; ISOLEUCINE; PHENYLALANINE; PHENOXYETHANOL; CAPRYLYL GLYCOL; MALTODEXTRIN; LYSINE; HISTIDINE; GLUTAMIC ACID; GLYCINE; LEUCINE; ALOE VERA LEAF; SILICON DIOXIDE; SODIUM ASCORBYL PHOSPHATE; TYROSINE; CHLORPHENESIN; TROLAMINE

Moisturizing body cream

Drug Facts

Active Ingredient:
Dimethicone 1.75%

Purpose
Skin Protectant

Uses
Temporarily protects and helps relieve chapped or cracked skin
beneficial for face, hands, body and legs

Warnings
For external use only.

When using this product, do not get into eyes

Do not use on

- deep or puncture wounds
- animal bites
- serious burns

Stop use and ask a doctor if:

- condition worsens
- symptoms last more than 7 days or clear up and occur again within a few days

Keep out of reach of children.
If swallowed, get medical help or contact a poison control center right away.

Directions
Apply cream liberally as needed

OTHER SAFETY INFORMATION

Store at 40-95ºF (4-35ºC).

Inactive ingredients
Alanine, Aleurites Moluccanus (Kukui) Seed Oil, Aloe
Barbadensis Leaf Juice, Arginine, Aspartic Acid, Bisabolol,
Butylene Glycol, Calcium Pantothenate (Vitamin B5), Caprylyl
Glycol, Carthamus Tinctorius (Safflower) Oleosomes,
Carthamus Tinctorius (Safflower) Seed Oil, Cetyl Alcohol,
Chlorphenesin, Dimethicone Crosspolymer, Dimethicone,
Disodium EDTA, Fragrance, Glutamic Acid, Glycerin, Glyceryl
Stearate, Glycine, Histidine, Isoleucine, Leucine, Lysine,
Maltodextrin, Niacinamide (Vitamin B3), PEG-100 Stearate,
Phenoxyethanol, Phenylalanine, Proline, Pyridoxine HCl
(Vitamin B6), Serine, Silica, Sodium Ascorbyl Phosphate
(Vitamin C), Sodium Hyaluronate, Sodium Starch
Octenylsuccinate, Stearic Acid, Threonine, Tocopheryl Acetate
(Vitamin E), Triethanolamine, Tyrosine, Valine, Water, Zingiber
Officinale (Ginger) Root Extract

Questions?
Call 1-800-777-4908

PACKAGE LABEL

NDC 68599-0218-4
McKesson
Thera
MOISTURIZING BODY CREAM
Everyday moisturizer and skin conditioner.
Single Patient Use
NET CONTENTS 4 fl oz (118 mL)
MFR # 53-CRM4

PACKAGE LABEL

NDC 68599-0218-8
McKesson
Thera
MOISTURIZING BODY CREAM
Everyday moisturizer and skin conditioner.
Single Patient Use
NET CONTENTS 32 fl oz (946 mL)
MFR # 53-CRM32

PACKAGE LABEL

NDC 68599-0218-1
McKesson
Thera
MOISTURIZING BODY CREAM
Refill for McKesson Pump Dispenser MFR # 53-1000.
NET CONTENTS 1000 mL (34 fl. oz.)
MFR # 53-CRM1000